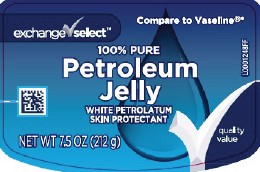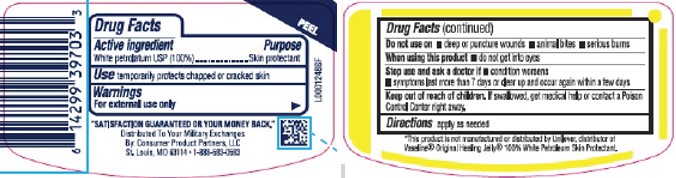 DRUG LABEL: Petroleum Skin Protectant
NDC: 55301-069 | Form: JELLY
Manufacturer: Your Military Exchanges
Category: otc | Type: HUMAN OTC DRUG LABEL
Date: 20260212

ACTIVE INGREDIENTS: PETROLATUM 1 g/1 g

Exchange Select 069.001/069AA
Petroleum Jelly

Active ingredient

White petrolatum USP (100%)

Purpose

Skin protectant

Use

temporarily protects chapped or cracked skin

Warnings

For external use only

Do not use on

- deep or puncture wounds
- animal bites
- serious burns

When using this product

- do not get into eyes

Stop use and ask a doctor if

- condition worsens
- symptoms last more than 7 days or clear up and occur again within a few days

Keep out of reach of children.

If swallowed, get medical help or contact a Poison Control Center right away.

Directions

apply as needed

Inactive Ingredient

none

Dislcaimer

*This product is not manufactured or distributed by Unilever, distributor of Vaseline®Original Healing Jelly100% White Petroleum Skin Protection.

Adverse Reactions

"SATISFACTION GUARANTEED OR YOUR MONEY BACK."

Distributed To Your Military Exchange

By: Consumer Product Partners, LLC

St. Lous, MO 63114 • 1-888-593-0593

principal display panel

Compare to Vaseline®*

exchange select™

100% PURE

Petroleum Jelly

WHITE PETROLATUM SKIN PROTECTANT

quality value

NET WT 7.5 OZ (212 g)